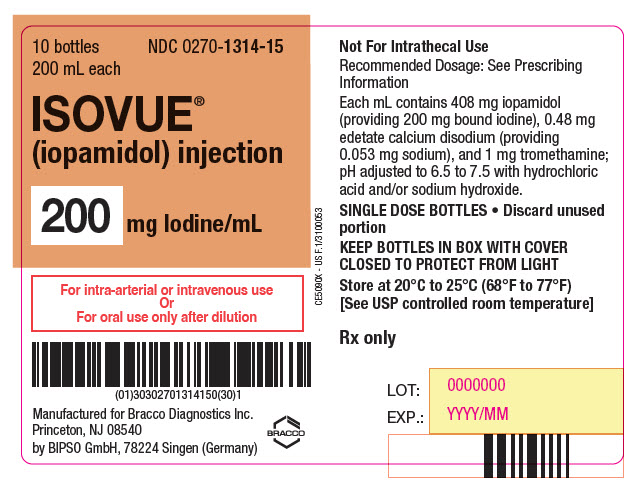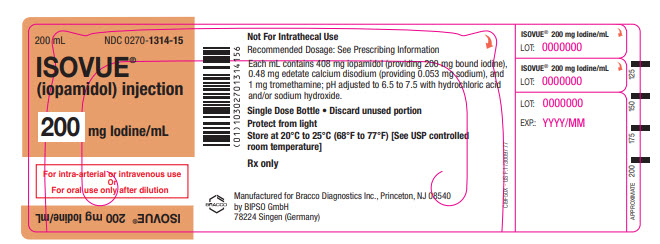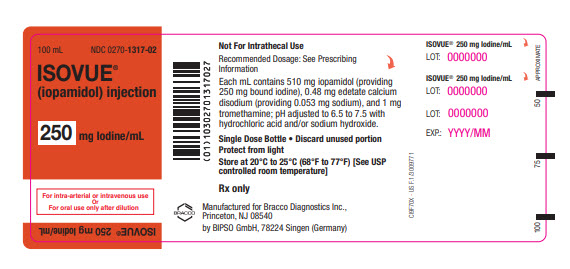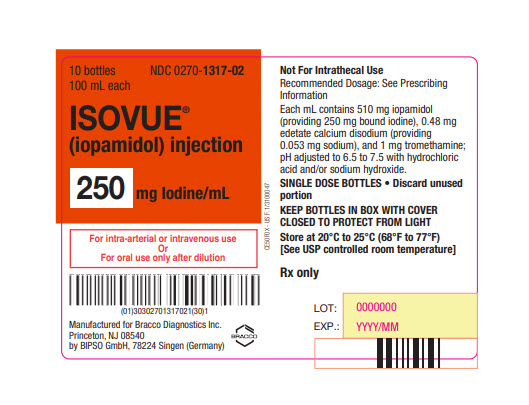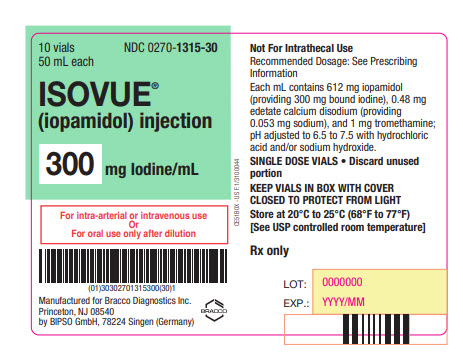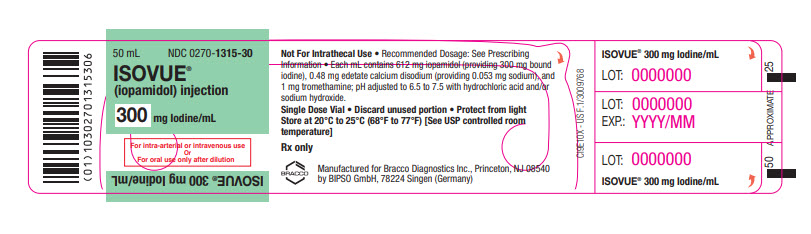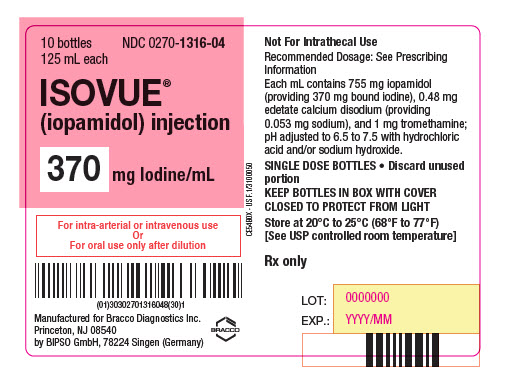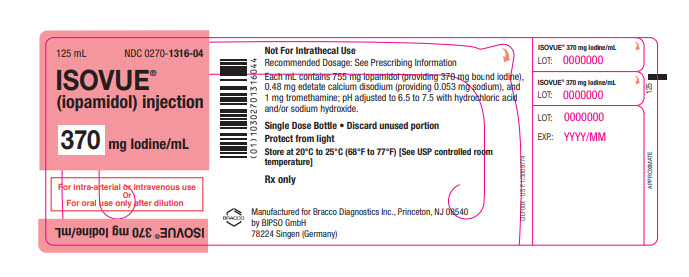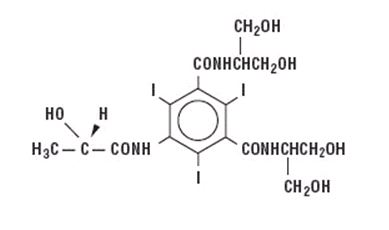 DRUG LABEL: ISOVUE
NDC: 0270-1315 | Form: INJECTION, SOLUTION
Manufacturer: BRACCO DIAGNOSTICS INC
Category: prescription | Type: HUMAN PRESCRIPTION DRUG LABEL
Date: 20251029

ACTIVE INGREDIENTS: IOPAMIDOL 612 mg/1 mL
INACTIVE INGREDIENTS: TROMETHAMINE 1 mg/1 mL; EDETATE CALCIUM DISODIUM 0.39 mg/1 mL

HIGHLIGHTS OF PRESCRIBING INFORMATION

These highlights do not include all the information needed to use ISOVUE safely and effectively. See full prescribing information for ISOVUE.
ISOVUE® (iopamidol) injection, for intra-arterial, intravenous, or oral use
Initial U.S. Approval: 1985

WARNING: RISKS ASSOCIATED WITH INTRATHECAL ADMINISTRATION

Intrathecal administration, even if inadvertent, can cause death, convulsions, cerebral hemorrhage, coma, paralysis, arachnoiditis, acute renal failure, cardiac arrest, seizures, rhabdomyolysis, hyperthermia, and brain edema. ISOVUE is for intra-arterial, intravenous, or oral use only. (5.1)

RECENT MAJOR CHANGES

Indications and Usage, Oral Procedures (1.3) | 10/2025
Dosage and Administration; - Recommended Dosage for Oral Procedures in Pediatric Patients and Adults (2.5) - Directions for Dilution of ISOVUE for Oral Administration (2.6) | 10/2025

1 INDICATIONS AND USAGE

ISOVUE is a radiographic contrast agent indicated for:

Intra-arterial Procedures † (1.1)

- Cerebral arteriography in adults
- Peripheral arteriography in adults
- Selective visceral arteriography and aortography in adults
- Coronary arteriography and cardiac ventriculography in adults
- Angiocardiography in pediatric patients

Intravenous Procedures† (1.2)

- Excretory urography in adults and pediatric patients
- Computed tomography (CT) of head and body in adults and pediatric patients
- Peripheral venography in adults

Oral Procedures† (1.3)

- CT of the abdomen and pelvis to delineate the gastrointestinal tract in adults and pediatric patients

†Specific concentrations are recommended for each type of imaging procedure. (2.2, 2.3, 2.4, 2.5)

2 DOSAGE AND ADMINISTRATION

- Individualize the volume and concentration according to the specific dosing tables accounting for factors such as age, body weight, size of the vessel, and the rate of blood flow within the vessel. (2.2, 2.3, 2.4, 2.5)
- See full prescribing information for important dosage and administration information and dilution instructions. (2.1, 2.6)

3 DOSAGE FORMS AND STRENGTHS

Injection: 200 mg Iodine/mL, 250 mg Iodine/mL, 300 mg Iodine/mL, and 370 mg Iodine/mL in single-dose vials or bottles(3)

4 CONTRAINDICATIONS

None (4)

5 WARNINGS AND PRECAUTIONS

- Hypersensitivity Reactions: Life-threatening or fatal reactions can occur. Always have emergency resuscitation equipment and trained personnel available. (5.2)
- Acute Kidney Injury: Acute injury including renal failure can occur. Use the lowest dose and maintain adequate hydration to minimize risk. (5.3)
- Cardiovascular Adverse Reactions: Hemodynamic disturbances including shock and cardiac arrest may occur during or after ISOVUE administration. (5.4)
- Thyroid Dysfunction in Pediatric Patients 0 Years to 3 Years of Age: Individualize thyroid function monitoring based on risk factors such as prematurity. (5.8)

6 ADVERSE REACTIONS

Most common adverse reactions (incidence >1%) are pain, hot flashes, burning sensation, nausea, and warmth (6.1)

To report SUSPECTED ADVERSE REACTIONS, contact Bracco Diagnostics Inc. at 1-800-257-5181 or FDA at 1-800-FDA-1088 or www.fda.gov/medwatch.

8 USE IN SPECIFIC POPULATIONS

Lactation: A lactating woman may pump and discard breast milk for 10 hours after ISOVUE administration. (8.2)

FULL PRESCRIBING INFORMATION

WARNING: RISKS ASSOCIATED WITH INTRATHECAL ADMINISTRATION

Intrathecal administration of ISOVUE, even if inadvertent, can cause death, convulsions, cerebral hemorrhage, coma, paralysis, arachnoiditis, acute renal failure, cardiac arrest, seizures, rhabdomyolysis, hyperthermia, and brain edema [see Warnings and Precautions (5.1)]. ISOVUE is for intra-arterial, intravenous, or oral use only [see Dosage and Administration (2.2, 2.3, 2.4, 2.5)].

1 INDICATIONS AND USAGE

1.1 Intra-arterial Procedures†

ISOVUE is indicated for:

- Cerebral arteriography in adults
- Peripheral arteriography in adults
- Selective visceral arteriography and aortography in adults
- Coronary arteriography and cardiac ventriculography in adults
- Angiocardiography in pediatric patients

1.2 Intravenous Procedures†

ISOVUE is indicated for:

- Excretory urography in adults and pediatric patients
- Computerized tomography (CT) of the head and body in adults and pediatric patients
- Peripheral venography in adults

†Specific concentrations of ISOVUE are recommended for each type of imaging procedure [see Dosage and Administration (2.2, 2.3, 2.4)].

1.3 Oral Procedures†

ISOVUE is indicated for:

- CT of the abdomen and pelvis to delineate the gastrointestinal tract in adults and pediatric patients

†Specific concentrations of ISOVUE are recommended for each type of imaging procedure [see Dosage and Administration (2.2, 2.3, 2.4, 2.5)].

2 DOSAGE AND ADMINISTRATION

2.1 Important Dosing and Administration Information

- ISOVUE is for intra-arterial or intravenous use only and must not be administered intrathecally [see Warnings and Precautions (5.1)].
- Specific concentrations of ISOVUE are recommended for each type of imaging procedure [see Dosage and Administration (2.2, 2.3, 2.4, 2.5)].
- Individualize the volume, concentration, and injection rate of ISOVUE according to the specific dosing tables [see Dosage and Administration (2.2, 2.3, 2.4, 2.5)]. Consider factors such as: age, body weight, blood vessel size and blood flow rate, anticipated pathology and degree and extent of opacification required, structures or area to be examined, concomitant medical conditions, imaging equipment, and technique to be employed.
- Hydrate patients before and after ISOVUE administration [see Warnings and Precautions (5.3)].
- Use aseptic technique for all handling and administration of ISOVUE.
- ISOVUE may be administered at either body temperature (37°C, 98.6°F) or room temperature (20°C to 25°C, 68°F to 77°F).
- Visually inspect ISOVUE for particulate matter or discoloration before administration. Do not administer ISOVUE if particulate matter or discolorations are observed.
- Do not mix ISOVUE with other drugs or inject in intravenous lines containing other drugs or total nutritional admixtures.
- ISOVUE single-dose containers are intended for one procedure only. Discard any unused portion.

2.2 Recommended Dosage for Intra-arterial Procedures in Adults

The recommended doses for intra-arterial procedures in adults are shown in Table 1.

Table 1: Recommended Concentrations and Volumes of ISOVUE for Intra-arterial Procedures in Adults
Imaging Procedure | Concentration (mg Iodine/mL) | Volume to Administer per Single Injection for Selected Injection Sites | Maximum Cumulative Total Dose
Cerebral Arteriography | 300 | 8 mL to 12 mL by carotid puncture or transfemoral catheterization | 90 mL
Peripheral Arteriography | 300 | - 5 mL to 40 mL into the femoral artery or subclavian artery - 25 mL to 50 mL into the aorta for a distal runoff | 250 mL
Selective Visceral Arteriography and Aortography | 370 | - Up to 10 mL for the renal arteries - Up to 50 mL into the larger vessels such as the aorta or celiac artery | 225 mL
Coronary Arteriography and Cardiac Ventriculography | 370 | - 2 mL to 10 mL for selective coronary artery injection - 25 mL to 50 mL for cardiac ventriculography or for nonselective opacification of multiple coronary arteries following injection at the aortic root | 200 mL

2.3 Recommended Dosage for Intravenous Procedures in Adults

The recommended doses for intravenous procedures in adults are shown in Table 2.

Table 2: Recommended Concentrations and Volumes of ISOVUE for Intravenous Procedures in Adults
Imaging Procedure | Concentration (mg Iodine/mL) | Volume to Administer
Excretory Urography | 250 | 50 mL to 100 mL by rapid injection
Excretory Urography | 300 | 50 mL by rapid injection
Excretory Urography | 370 | 40 mL by rapid injection
CT of the Head | 250 | 130 mL to 240 mL
CT of the Head | 300 | 100 mL to 200 mL
CT of the Body | 250 | 130 mL to 240 mL by rapid infusion or bolus injection
CT of the Body | 300 | 100 mL to 200 mL by rapid infusion or bolus injection
CT of the Body | 370 | 80 mL to 160 mL by rapid infusion or bolus injection
Peripheral Venography | 200 | 25 mL to 150 mL per lower extremity; the maximum total dose is 350 mL

2.4 Recommended Dosage for Intra-arterial and Intravenous Procedures in Pediatric Patients

The recommended doses for intra-arterial and intravenous procedures in pediatric patients are shown in Table 3.

Table 3: Recommended Concentrations and Volumes per Body Weight of ISOVUE for Intra- arterial and Intravenous Procedures in Pediatric Patients
Imaging Procedure | Concentration (mg Iodine/mL) | Volume per Body Weight to Administer | Maximum Dose
Intra-arterial Procedures
Angiocardiography | 370 | 0.5 mL/kg to 2 mL/kg per single injection | Maximum Cumulative Dose by Weight; - Neonates: 5 mL/kg - Aged 4 weeks and older: 8 mL/kg - Do not exceed maximum cumulative doses by age below.; Maximum Cumulative Dose by Age; - <2 years 40 mL - 2 years to 4 years 50 mL - 5 years to 9 years 100 mL - 10 years to 18 years 125 mL
Intravenous Procedures
Excretory Urography | 250 | 1.2 mL/kg to 3.6 mL/kg | 120 mL
Excretory Urography | 300 | 1 mL/kg to 3 mL/kg | 100 mL
CT of the Head and Body | 250 | 1.2 mL/kg to 3.6 mL/kg | 120 mL
CT of the Head and Body | 300 | 1 mL/kg to 3 mL/kg | 100 mL

2.5 Recommended Dosage for Oral Procedures in Pediatric Patients and Adults

- The recommended concentration of diluted ISOVUE is either 6 mg iodine/mL or 9 mg iodine/mL administered orally as shown in Table 4.
- See Table 5 for dilution instructions of ISOVUE [see Dosage and Administration (2.6)]

Table 4: Recommended Volumes of Diluted ISOVUE for Oral Administration for CT of the Abdomen and Pelvis in Pediatric Patients and Adults
Age | Volume of Diluted ISOVUE‡ to Administer | Administration Instructions
Pediatric patients less than 3 years of age | 50 mL to 300 mL | Administer the oral dose approximately 60 minutes before beginning the CT procedure.
Pediatric patients 3 years to 5 years of age | 300 mL to 360 mL | Administer the oral dose approximately 60 minutes before beginning the CT procedure.
Pediatric patients 6 years to 11 years of age | 360 mL to 500 mL | Administer the oral dose approximately 60 minutes before beginning the CT procedure.
Pediatric patients 12 years of age and older | 500 mL to 1,000 mL | Administer the oral dose approximately 60 minutes before beginning the CT procedure.
Adults | 500 mL to 1,000 mL | Administer the oral dose approximately 60 minutes before beginning the CT procedure.

‡ Prepare diluted ISOVUE solution to a concentration of either 6 mg iodine/mL or 9 mg iodine/mL according to Table 5 [see Dosage and Administration (2.6)].

2.6 Directions for Dilution of ISOVUE for Oral Administration

- Dilute ISOVUE to 6 mg iodine/mL or 9 mg iodine/mL in water or clear liquids such as apple juice according to Table 5.
- Use diluted ISOVUE immediately.
- Discard any unused portion after the procedure.

Table 5: Volumes of ISOVUE and Added Liquid to Dilute ISOVUE for Oral Administration for CT of the Abdomen and Pelvis
Final Concentration of Diluted ISOVUE (mg Iodine/mL) | ISOVUE |  | Volume of Added Liquid§ (mL)
Final Concentration of Diluted ISOVUE (mg Iodine/mL) | Concentration (mg Iodine/mL) | Volume (mL) | Volume of Added Liquid§ (mL)
6 | 200 | 30 | 970
6 | 250 | 24 | 976
6 | 300 | 20 | 980
6 | 370 | 16 | 984
9 | 200 | 45 | 955
9 | 250 | 36 | 964
9 | 300 | 30 | 970
9 | 370 | 24 | 976

§Use water or clear liquids such as apple juice.

3 DOSAGE FORMS AND STRENGTHS

Injection: Clear, colorless to pale yellow solution available in the following concentrations of iodine:

Concentration (mg Iodine/mL) | Package Size | Package Type
200 | 200 mL | Single-Dose Bottle
250 | 100 mL | Single-Dose Bottle
300 | 30 mL and 50 mL | Single-Dose Vial
300 | 100 mL and 150 mL | Single-Dose Bottle
370 | 50 mL | Single-Dose Vial
370 | 75 mL, 100 mL, 125 mL, and 150 mL | Single-Dose Bottle

4 CONTRAINDICATIONS

None.

5 WARNINGS AND PRECAUTIONS

5.1 Risks Associated with Intrathecal Administration

Intrathecal administration, even if inadvertent, can cause death, convulsions, cerebral hemorrhage, coma, paralysis, arachnoiditis, acute renal failure, cardiac arrest, seizures, rhabdomyolysis, hyperthermia, and brain edema. ISOVUE is for intra-arterial or intravenous use only and must not be administered intrathecally [see Dosage and Administration (2.1)].

5.2 Hypersensitivity Reactions

ISOVUE can cause life-threatening or fatal hypersensitivity reactions including anaphylaxis. Manifestations include respiratory arrest, laryngospasm, bronchospasm, angioedema, and shock [see Adverse Reactions (6.2)]. Most severe reactions develop shortly after the start of injection (e.g., within 1 to 3 minutes), but delayed reactions can also occur. There is increased risk of hypersensitivity reactions in patients with a history of previous reactions to contrast agents, and allergic disorders (i.e., bronchial asthma, allergic rhinitis, and food allergies) or other hypersensitivities.

Premedication with antihistamines or corticosteroids to avoid or minimize possible allergic reactions does not prevent serious life-threatening reactions but may reduce both their incidence and severity. Obtain a history of allergy, hypersensitivity, or hypersensitivity reactions to iodinated contrast agents and always have emergency resuscitation equipment and trained personnel available prior to ISOVUE administration. Monitor all patients for hypersensitivity reactions.

5.3 Acute Kidney Injury

Acute kidney injury, including renal failure, may occur after ISOVUE administration. Risk factors include: pre-existing renal insufficiency, dehydration, diabetes mellitus, congestive heart failure, advanced vascular disease, elderly age, concomitant use of nephrotoxic or diuretic medications, multiple myeloma or other paraproteinemias, and repetitive or large doses of ISOVUE.

Use the lowest necessary dose of ISOVUE in patients with renal impairment. Adequately hydrate patients prior to and following ISOVUE administration. Do not use laxatives, diuretics, or preparatory dehydration prior to ISOVUE administration.

5.4 Cardiovascular Adverse Reactions

ISOVUE increases the circulatory osmotic load and may induce acute or delayed hemodynamic disturbances in patients with congestive heart failure, severely impaired renal function, combined renal and hepatic disease, and combined renal and cardiac disease, particularly when repetitive or large doses are administered. Fatal cardiovascular reactions have occurred mostly within 10 minutes of ISOVUE injection; the main feature was cardiac arrest with cardiovascular disease as the main underlying factor. Hypotensive collapse and shock have occurred. Cardiac decompensation, serious arrhythmias, and myocardial ischemia or infarction can occur during coronary arteriography and ventriculography.

The administration of ISOVUE may cause pulmonary edema in patients with heart failure. Based upon published reports, deaths associated with the administration of iodinated contrast agents range from 6.6 per 1 million (0.00066 percent) to 1 in 10,000 patients (0.01 percent). Use the lowest necessary dose of ISOVUE in patients with congestive heart failure and always have emergency resuscitation equipment and trained personnel available. Monitor all patients for severe cardiovascular reactions.

5.5 Thromboembolic Events

Serious, in some cases fatal, thromboembolic events, including myocardial infarction and stroke, can occur during angiographic procedures. During these procedures, increased thrombosis and activation of the complement system occurs. Risk factors for developing thromboembolic events include: length of procedure, catheter and syringe material, underlying disease state, and concomitant medications.

To minimize thromboembolic events, use meticulous angiographic techniques and minimize the length of the procedure. Avoid blood remaining in contact with syringes containing iodinated contrast agents, which increases risk of clotting. Avoid angiocardiography in patients with homocystinuria because of the risk of inducing thrombosis and embolism.

5.6 Extravasation and Injection Site Reactions

Extravasation can occur with ISOVUE administration, particularly in patients with severe arterial or venous disease. Inflammation, blistering, skin necrosis, and compartment syndrome have been reported following extravasation. In addition, injection site reactions such as pain and swelling at the injection site can also occur [see Adverse Reactions (6.2)]. Ensure intravascular placement of catheters prior to injection. Monitor patients for extravasation and advise patients to seek medical care for progression of symptoms.

5.7 Thyroid Storm in Patients with Hyperthyroidism

Thyroid storm has occurred after the intravascular use of iodinated agents in patients with hyperthyroidism or with an autonomously functioning thyroid nodule. Evaluate the risk in such patients before use of ISOVUE.

5.8 Thyroid Dysfunction in Pediatric Patients 0 Years to 3 Years of Age

Thyroid dysfunction characterized by hypothyroidism or transient thyroid suppression has been reported after both single exposure and multiple exposures to iodinated contrast agents in pediatric patients 0 years to 3 years of age.

Younger age, very low birth weight, prematurity, underlying medical conditions affecting thyroid function, admission to neonatal or pediatric intensive care units, and congenital cardiac conditions are associated with an increased risk of hypothyroidism after iodinated contrast agent exposure. Pediatric patients with congenital cardiac conditions may be at greatest risk given that they often require high doses of contrast during invasive cardiac procedures.

An underactive thyroid during early life may be harmful for cognitive and neurological development and may require thyroid hormone replacement therapy. After exposure to iodinated contrast agents, individualize thyroid function monitoring based on underlying risk factors, especially in term and preterm neonates.

5.9 Hypertensive Crisis in Patients with Pheochromocytoma

Hypertensive crisis in patients with pheochromocytoma has occurred with iodinated contrast agents. Closely monitor patients when administering ISOVUE if pheochromocytoma or catecholamine-secreting paragangliomas are suspected. Inject the minimum amount of ISOVUE necessary and have measures for treatment of hypertensive crisis readily available.

5.10 Sickle Cell Crisis in Patients with Sickle Cell Disease

Iodinated contrast agents can promote sickling in individuals who are homozygous for sickle cell disease. Hydrate patients prior to and following ISOVUE administration and use only if the necessary imaging information cannot be obtained with alternative imaging modalities.

5.11 Severe Cutaneous Adverse Reactions

Severe cutaneous adverse reactions (SCAR) may develop from 1 hour to several weeks after intravascular contrast agent administration. These reactions include Stevens-Johnson syndrome and toxic epidermal necrolysis (SJS/TEN), acute generalized exanthematous pustulosis (AGEP), and drug reaction with eosinophilia and systemic symptoms (DRESS). Reaction severity may increase and time to onset may decrease with repeat administration of a contrast agent; prophylactic medications may not prevent or mitigate severe cutaneous adverse reactions. Avoid administering ISOVUE to patients with a history of a severe cutaneous adverse reaction to ISOVUE.

5.12 Interference with Laboratory Tests

ISOVUE can interfere with protein-bound iodine test [see Drug Interactions (7.2)].

6 ADVERSE REACTIONS

The following adverse reactions are described in greater detail in other sections:

- Risks Associated with Intrathecal Administration [see Warnings and Precautions (5.1)]
- Hypersensitivity Reactions [see Warnings and Precautions (5.2)]
- Acute Kidney Injury [see Warnings and Precautions (5.3)]
- Cardiovascular Adverse Reactions [see Warnings and Precautions (5.4)]
- Thromboembolic Events [see Warnings and Precautions (5.5)]
- Extravasation and Injection Site Reactions [see Warnings and Precautions (5.6)]
- Thyroid Dysfunction in Pediatric Patients 0 to 3 Years of Age [see Warnings and Precautions (5.8)]
- Severe Cutaneous Adverse Reactions [see Warnings and Precautions (5.11)]

6.1 Clinical Trials Experience

Because clinical trials are conducted under widely varying conditions, adverse reaction rates observed in the clinical trials of a drug cannot be directly compared to rates in the clinical trials of another drug and may not reflect the rates observed in practice.

Adverse Reactions in Adults

The safety of ISOVUE was evaluated in 2,246 adult patients receiving ISOVUE by intra-arterial or intravenous route in clinical studies. Table 4 shows the common adverse reactions (>1%).

Table 6: Adverse Reactions Reported in >1% of Patients Receiving Intra-arterial or Intravenous Injection of ISOVUE in Clinical Studies
Adverse Reaction | ISOVUE (N=2,246) %
Pain | 2.8
Hot flashes | 1.5
Burning sensation | 1.4
Nausea | 1.2
Warmth | 1.1

The following adverse reactions occurred in ≤ 1% of patients receiving intra-arterial or intravenous injection of ISOVUE:

Cardiovascular disorders: tachycardia, hypotension, hypertension, myocardial ischemia, circulatory collapse, S-T segment depression, bigeminy, extrasystoles, ventricular fibrillation, angina pectoris, bradycardia, transient ischemic attack, thrombophlebitis

Gastrointestinal disorders: vomiting, anorexia

General disorders: headache, fever, chills, excessive sweating, back spasm

Nervous system disorders: vasovagal reaction, tingling in arms, grimace, faintness

Renal and urinary disorders: urinary retention

Respiratory: throat constriction, dyspnea, pulmonary edema

Skin and subcutaneous tissues: rash, urticaria, pruritus, flushing

Special senses: taste alterations, nasal congestion, visual disturbances

Adverse Reactions from Intra-arterial Use in Pediatric Patients

In a clinical trial with 76 pediatric patients undergoing angiocardiography, two adverse reactions (2.6%) were reported: worsening cyanosis and worsening peripheral perfusion.

Adverse Reactions from Oral Use in Adult and Pediatric Patients

There were no new adverse reactions from oral use of ISOVUE in adult and pediatric patients [see Clinical Studies (14)].

6.2 Postmarketing Experience

The following adverse reactions have been identified during post approval use of ISOVUE. Because the reactions are reported voluntarily from a population of uncertain size, it is not always possible to reliably estimate their frequency or to establish a causal relationship to drug exposure.

Blood and lymphatic system disorders: thrombocytopenia

Cardiovascular disorders: cardiopulmonary arrest, cardiac decompensation, arrhythmias, myocardial infarction, shock, electrocardiographic changes (e.g., increased QTc, increased R-R, increased T- wave amplitude), decreased systolic pressure, deep vein thrombosis, arterial spasms, vasodilation, chest pain, pallor

Endocrine disorders: hyperthyroidism, hypothyroidism

Eye disorders: lacrimation increased, conjunctivitis, eye pruritus, transient blindness, visual disturbance, photophobia

Gastrointestinal disorders: retching, abdominal pain, salivary hypersecretion, salivary gland enlargement

General disorders and administration site conditions: injection site pain, malaise

Immune system disorders: anaphylaxis characterized by cardiovascular, respiratory, and cutaneous manifestations (e.g., chest tightness, laryngeal edema, periorbital edema, facial edema); delayed hypersensitivity reactions including generalized maculopapular rash, erythema, pruritus, localized blistering, skin peeling

Musculoskeletal disorders: compartment syndrome following extravasation, muscle spasm, musculoskeletal pain, muscular weakness

Nervous system disorders: coma, seizure, tremors, syncope, depressed level of consciousness or loss of consciousness, encephalopathy

Psychiatric disorders: confusional state

Respiratory system disorders: respiratory arrest, respiratory failure, acute respiratory distress syndrome, respiratory distress, apnea, asthma, sneezing, choking, laryngeal edema, bronchospasm, rhinitis

Skin and subcutaneous tissue disorders: Stevens-Johnson syndrome and toxic epidermal necrolysis (SJS/TEN), acute generalized exanthematous pustulosis (AGEP), erythema multiforme and drug reaction with eosinophilia and systemic symptoms (DRESS), skin necrosis, face edema

7 DRUG INTERACTIONS

7.1 Drug-Drug Interactions

Metformin

In patients with renal impairment, metformin can cause lactic acidosis. Iodinated contrast agents appear to increase the risk of metformin-induced lactic acidosis, possibly as a result of worsening renal function. Stop metformin at the time of, or prior to, ISOVUE administration in patients with an eGFR between 30 and 60 mL/min/1.73 m^2; in patients with a history of hepatic impairment, alcoholism, or heart failure; or in patients who will be administered intra-arterial iodinated contrast agents. Re-evaluate eGFR 48 hours after the imaging procedure and reinstitute metformin use only after renal function is stable.

Radioactive Iodine

Administration of ISOVUE may interfere with thyroid uptake of radioactive iodine (I-131 and I-123) and decrease therapeutic and diagnostic efficacy. Avoid thyroid therapy or testing for up to 6 weeks post ISOVUE.

7.2 Drug-Laboratory Test Interactions

Protein-Bound Iodine Test

Iodinated contrast agents, including ISOVUE, will temporarily increase protein-bound iodine in blood. Avoid protein-bound iodine test for at least 16 days following administration of ISOVUE. However, thyroid function tests that do not depend on iodine estimations, e.g., triiodothyronine (T3) resin uptake and total or free thyroxine (T4) assays are not affected.

8 USE IN SPECIFIC POPULATIONS

8.1 Pregnancy

Risk Summary

Available data from published literature and postmarketing cases from decades of use with iopamidol during pregnancy have not identified a drug-associated risk of major birth defects, miscarriage, or other adverse maternal or fetal outcomes. Iopamidol crosses the placenta and reaches fetal tissues in small amounts (see Data). In animal reproduction studies, no adverse developmental outcomes were observed with intravenous administration of iopamidol to pregnant rats and rabbits during organogenesis at doses up to 2.7 and 1.4 times, respectively, the maximum recommended human dose (see Data).

The background risk of major birth defects and miscarriage for the indicated population is unknown. All pregnancies have a background risk of birth defect, loss, or other adverse outcomes. In the U.S. general population, the estimated background risk of major birth defects and miscarriage in clinically recognized pregnancies is 2 to 4% and 15 to 20%, respectively.

Data

Human Data

Literature reports show that intravenously administered iopamidol crosses the placenta and is visualized in the digestive tract of exposed infants after birth.

Animal Data

Iopamidol did not affect fetal development and did not induce teratogenic changes in the offspring in either rats or rabbits at the following dose levels tested: 600 mg, 1,500 mg, or 4,000 mg iodine/kg in rats, administered intravenously once a day during days 6 through 15 of pregnancy; 300 mg, 800 mg, or 2,000 mg iodine/kg in rabbits, administered intravenously once a day during days 6 through 18 of pregnancy.

8.2 Lactation

Risk Summary

There are no data on the presence of iopamidol in human milk, the effects on the breastfed infant, or the effects on milk production. Iodinated contrast agents are present unchanged in human milk in very low amounts, with poor absorption from the gastrointestinal tract of a breastfed infant. The developmental and health benefits of breastfeeding should be considered along with the mother's clinical need for ISOVUE and any potential adverse effects on the breastfed infant from ISOVUE or from the underlying maternal condition.

Clinical Considerations

Interruption of breastfeeding after exposure to iodinated contrast agents is not necessary because the potential exposure of the breastfed infant to iodine is small. However, a lactating woman may consider interrupting breastfeeding and pumping and discarding breast milk for 10 hours (approximately 5 half- lives) after ISOVUE administration in order to minimize drug exposure to a breastfed infant.

8.4 Pediatric Use

The safety and effectiveness of ISOVUE have been established in pediatric patients for intra-arterial administration for angiocardiography and for intravenous administration for excretory urography and contrast computed tomography (head and body).

The safety and effectiveness of ISOVUE have been established in pediatric patients for oral administration for CT of the abdomen and pelvis to delineate the gastrointestinal tract. Use of ISOVUE for this indication is supported by evidence from an adequate and well-controlled clinical study in adults (n=152) and pediatric patients 3 to 16 years of age (n=66) who underwent CT of the abdomen and pelvis with oral administration of ISOVUE and from additional safety data from post-approval use of enteral iopamidol in adult and pediatric patients [see Adverse Reactions (6.2)] and Clinical Studies (14)].

Pediatric patients at higher risk of experiencing adverse reactions during and after contrast medium administration may include those having asthma, sensitivity to medication or allergens, cyanotic heart disease, congestive heart failure, or serum creatinine greater than 1.5 mg/dL, or those less than 12 months of age.

Thyroid function tests indicative of thyroid dysfunction, characterized by hypothyroidism or transient thyroid suppression have been reported following iodinated contrast media administration in pediatric patients, including term and preterm neonates; some patients were treated for hypothyroidism. After exposure to iodinated contrast media, individualize thyroid function monitoring in pediatric patients 0 years to 3 years of age based on underlying risk factors, especially in term and preterm neonates [see Warning and Precautions (5.8) and Adverse Reactions (6.2)].

The safety and effectiveness of ISOVUE for cerebral, peripheral, and selective visceral arteriography, aortography, coronary arteriography, cardiac ventriculography, and peripheral venography have not been established in pediatric patients.

8.5 Geriatric Use

Iopamidol is excreted by the kidney, and the risk of adverse reactions to ISOVUE may be greater in patients with renal impairment. Because patients 65 years of age and older are more likely to have renal impairment, care should be taken in dose selection, and it may be useful to monitor renal function [see Warnings and Precautions (5.3) and Use in Specific Populations [8.6]).

8.6 Renal Impairment

The clearance of iopamidol decreases with increasing degree of renal impairment and results in delayed opacification of the urinary system. In addition, preexisting renal impairment increases the risk for acute kidney injury [see Warnings and Precautions (5.3)]. Iopamidol can be removed by dialysis.

10 OVERDOSAGE

The manifestations of overdosage are life-threatening and affect mainly the pulmonary and cardiovascular systems. Treatment of an overdose is directed toward support of all vital functions and the prompt institution of symptomatic therapy. Iopamidol can be removed by dialysis.

11 DESCRIPTION

ISOVUE (iopamidol) injection is a radiographic contrast agent for intra-arterial or intravenous use.

Iopamidol is designated chemically as (S)-N,N’-bis[2-hydroxy-1-(hydroxymethyl)-ethyl]-2,4,6-triiodo-5- lactamidoisophthalamide with a molecular weight of 777.09, an empirical formula of C17H22I3N3O8, and the following structural formula:

ISOVUE is a sterile, clear, colorless to pale yellow solution available in four concentrations of iodine:

- ISOVUE 200 mg iodine/mL: Each mL contains 408 mg iopamidol (providing 200 mg organically bound iodine) and the following inactive ingredients: 0.26 mg edetate calcium disodium (providing 0.029 mg (0.001 mEq) sodium) and 1 mg tromethamine.
- ISOVUE 250 mg iodine/mL: Each mL contains 510 mg iopamidol (providing 250 mg organically bound iodine) and the following inactive ingredients: 0.33 mg edetate calcium disodium (providing 0.036 mg (0.002 mEq) sodium) and 1 mg tromethamine.
- ISOVUE 300 mg iodine/mL: Each mL contains 612 mg iopamidol (providing 300 mg organically bound iodine) and the following inactive ingredients: 0.39 mg edetate calcium disodium (providing 0.043 mg (0.002 mEq) sodium) and 1 mg tromethamine.
- ISOVUE 370 mg iodine/mL: Each mL contains 755 mg iopamidol (providing 370 mg organically bound iodine) and the following inactive ingredients: 0.48 mg edetate calcium disodium (providing 0.053 mg (0.002 mEq) sodium) and 1 mg tromethamine.

The pH of ISOVUE has been adjusted to 6.5 to 7.5 with hydrochloric acid and/or sodium hydroxide.

Physicochemical characteristics are shown in Table 5. ISOVUE is hypertonic as compared to plasma and cerebrospinal fluid (approximately 285 and 301 mOsm/kg water, respectively).

Table 7: Physicochemical Characteristics of ISOVUE
Concentration (mg Iodine/mL) | 200 | 250 | 300 | 370
Osmolality @ 37°C (mOsm/kg water) | 413 | 524 | 616 | 796
Viscosity (cP) @ 37°C | 2.0 | 3.0 | 4.7 | 9.4
Viscosity (cP) @ 20°C | 3.3 | 5.1 | 8.8 | 20.9
Specific Gravity @ 37°C | 1.227 | 1.281 | 1.339 | 1.405

12 CLINICAL PHARMACOLOGY

12.1 Mechanism of Action

The iodine atoms in iopamidol provide attenuation of X-rays in direct proportion to the concentration of iopamidol. Since concentration changes over time, iopamidol provides time-dependent image contrast, which may assist in visualizing body structures.

In imaging of the body, iodinated contrast agents diffuse from the vessels into the extravascular space. In normal brain with an intact blood-brain barrier, contrast does not diffuse into the extravascular space. In patients with a disrupted blood-brain barrier, contrast agent accumulates in the extravascular space in the region of disruption.

12.2 Pharmacodynamics

Following administration of ISOVUE, the degree of enhancement is related to the iodine concentration in the tissue of interest. However, the exposure-response relationships and time course of pharmacodynamic response of iopamidol have not been fully characterized.

12.3 Pharmacokinetics

Absorption

Following oral administration, iopamidol is minimally absorbed from the gastrointestinal tract. Less than 1% of the administered dose is recovered in urine within 12 hours post-dose.

Distribution

After intravascular administration, plasma concentrations of iodine fall within 5 to 10 minutes due to distribution into the vascular and extracellular fluid compartments. Equilibration with the extracellular compartments is reached in about 10 minutes.

The apparent volume of distribution suggests that iopamidol is distributed evenly between blood and extracellular fluid. Iopamidol may be visualized in the renal parenchyma within 30 to 60 seconds following rapid intravenous administration. Iopamidol did not bind to serum or plasma proteins at 1 hour after administration.

Elimination

The plasma half-life is approximately 2 hours; the half-life is not dose dependent.

Metabolism

Iopamidol does not undergo significant metabolism, deiodination, or biotransformation.

Excretion

Iopamidol is excreted primarily through the kidneys. In patients with normal renal function, the cumulative urinary excretion for iopamidol, expressed as a percentage of administered intravenous dose, is approximately 35% to 40% at 60 minutes, 80% to 90% at 8 hours, and 90% or greater in the 72- to 96- hour period after administration. In patients with normal renal function, approximately 1% or less of the administered dose appears in cumulative 72- to 96-hour fecal samples.

13 NONCLINICAL TOXICOLOGY

13.1 Carcinogenesis, Mutagenesis, Impairment of Fertility

Long-term studies in animals have not been performed with iopamidol to evaluate carcinogenic potential. No evidence of genetic toxicity was obtained in in vitro tests. In animal reproduction studies performed on rats, intravenously administered iopamidol did not induce adverse effects on fertility or general reproductive performance.

14 CLINICAL STUDIES

Oral Administration for CT of the Abdomen and Pelvis

The safety and effectiveness of orally administered ISOVUE for CT of the abdomen and pelvis were evaluated in a study in which previously collected images were prospectively re-read from 218 consecutive patients, including 152 adult patients and 66 pediatric patients aged 3 to 16 years, who underwent CT of the abdomen and pelvis after oral ISOVUE administration. Patients who received ISOVUE by enteral tube, who had suspected bowel obstruction, or who had history of surgery altering bowel transit time were excluded. CT images were evaluated by three blinded, independent readers who assessed delineation of each of five segments of the gastrointestinal tract (stomach, duodenum, jejunum, proximal ileum, and distal ileum) using a three-point scale (poor, sufficient, good). Segments rated as sufficient or good were defined as having adequate anatomic delineation. Patients were considered to have adequate delineation if at least three of the five segments were rated as adequate.

All 218 patients had evaluable CT images. Patient age ranged from 3 years to 97 years, with a mean of 39 years. Patients were 55% female, 75% White, 9% Black or African American, 4% Asian, and <1% Native Hawaiian or Other Pacific Islander, with race not reported or unknown in 12% of patients. ISOVUE was also administered intravenously in 213 (98%) patients.

The percentage of patients with adequate anatomic delineation of the gastrointestinal tract was 77%, 81%, and 97% for the three readers with lower bounds of the 95% confidence intervals of 71%, 75%, and 94%, respectively.

16 HOW SUPPLIED/STORAGE AND HANDLING

How Supplied

ISOVUE (iopamidol) injection is a clear, colorless to pale yellow solution available in the following presentations:

Concentration (mg Iodine/mL) | Package Size | Package Type | Sale Unit | NDC
200 | 200 mL | Single-Dose Bottle | Carton of 10 | 0270-1314-15
250 | 100 mL | Single-Dose Bottle | Carton of 10 | 0270-1317-02
300 | 30 mL | Single-Dose Vial | Carton of 10 | 0270-1315-25
300 | 50 mL | Single-Dose Vial | Carton of 10 | 0270-1315-30
300 | 100 mL | Single-Dose Bottle | Carton of 10 | 0270-1315-35
300 | 150 mL | Single-Dose Bottle | Carton of 10 | 0270-1315-50
370 | 50 mL | Single-Dose Vial | Carton of 10 | 0270-1316-30
370 | 100 mL | Single-Dose Bottle | Carton of 10 | 0270-1316-35
370 | 125 mL | Single-Dose Bottle | Carton of 10 | 0270-1316-04
370 | 150 mL | Single-Dose Bottle | Carton of 10 | 0270-1316-37

Storage and Handling

Store at 20°C to 25°C (68°F to 77°F) [See USP controlled room temperature]. Protect from light.

17 PATIENT COUNSELING INFORMATION

Hypersensitivity Reactions

Advise the patient concerning the risk of hypersensitivity reactions that can occur both during and after ISOVUE administration. Advise the patient to report any signs or symptoms of hypersensitivity reactions during the procedure and to seek immediate medical attention for any signs or symptoms experienced after discharge [see Warnings and Precautions (5.2)].

Advise patients to inform their physician if they develop a rash after receiving ISOVUE [see Warnings and Precautions (5.11)].

Acute Kidney Injury

Advise the patient concerning appropriate hydration to decrease the risk of contrast induced kidney injury [see Warnings and Precautions (5.3)].

Extravasation

If extravasation occurs during injection, advise patients to seek medical care for progression of symptoms [see Warnings and Precautions (5.6)].

Thyroid Dysfunction

Advise parents/caregivers about the risk of developing thyroid dysfunction after ISOVUE administration. Advise parents/caregivers about when to seek medical care for their child to monitor for thyroid function [see Warnings and Precautions (5.8)].

Lactation

Advise a lactating woman that interruption of breastfeeding is not necessary, however, to minimize exposure to a breastfed infant, a lactating woman may consider pumping and discarding breast milk for 10 hours after ISOVUE administration [see Use in Specific Populations (8.2)].

Manufactured for:
Bracco Diagnostic Inc.
Princeton, NJ 08540

Manufactured by:
BIPSO GmbH
78224 Singen (Germany)

ISOVUE is a registered trademark of Bracco Diagnostics Inc.

Revised October 2025

Isovue 200: 200mL Bottle Label
NDC 0270-1314-15

Isovue 200:10x 200mL Box Label
NDC 0270-1314-15

Isovue 250: 100mL Bottle Label
NDC 0270-1317-02

Isovue 250: 10x 100mL Box label
NDC 0270-1317-02

Isovue 300: 10x 50mL Box label
NDC 0270-1315-30

Isovue 300: 50mL Vial Label
NDC 0270-1315-30

Isovue 370: 125mL Bottle label
NDC 0270-1316-04

Isovue 370: 10x 125mL Box Label
NDC 0270-1316-04